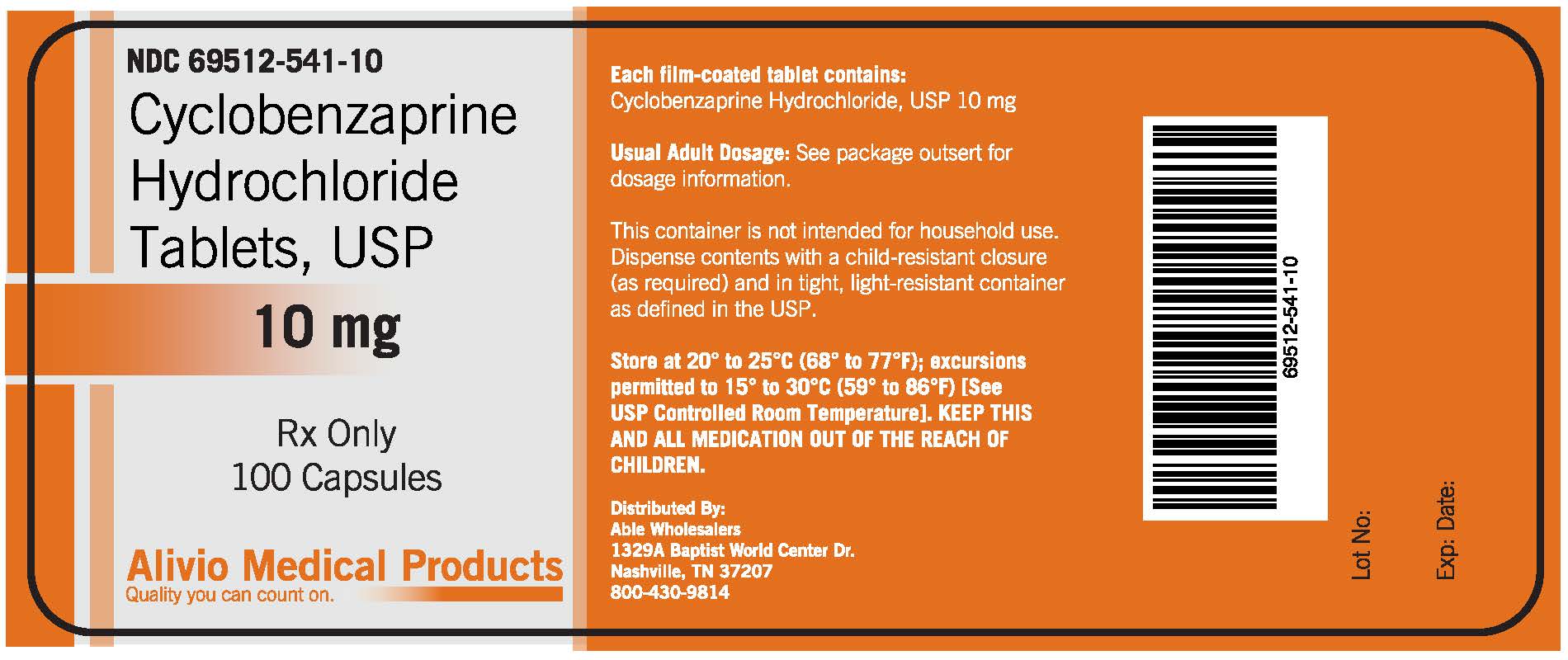 DRUG LABEL: CYCLOBENZAPRINE HYDROCHLORIDE
NDC: 69512-541 | Form: TABLET
Manufacturer: Alivio Medical Products, LLC
Category: prescription | Type: HUMAN PRESCRIPTION DRUG LABEL
Date: 20151015

ACTIVE INGREDIENTS: CYCLOBENZAPRINE HYDROCHLORIDE 10 mg/10 mg
INACTIVE INGREDIENTS: CROSCARMELLOSE SODIUM; D&C YELLOW NO. 10; FD&C BLUE NO. 2; FD&C YELLOW NO. 6; LACTOSE MONOHYDRATE; MAGNESIUM STEARATE; CELLULOSE, MICROCRYSTALLINE; POLYETHYLENE GLYCOLS; POLYVINYL ALCOHOL; SILICON DIOXIDE; TALC; TITANIUM DIOXIDE

Drug Facts

DESCRIPTION

Each film-coated tablet contains:

Cyclobenzaprine Hydrichloride, USP 10 mg

DESCRIPTION

Usual Adult Dosage:

See package outsert for dosage information

STORAGE AND HANDLING

This container is not intended for household use.

Dispense contents with a child-resistant closure

(as required) and in tight, light-resistant container

as defined in the USP.

Store at 20 to 25 C (68 to 77 F); excursions

permitted to 15 to 30 C (59 to 86 F) [See

USP Controlled Room Temperature]. KEEP THIS

AND ALL MEDICATION OUT OF THE REACH OF CHILDREN.

DESCRIPTION

Cyclobenzaprine hydrochloride, USP is a white, crystalline tricyclic amine salt with the empirical

formula C20H21N-HCl and a molecular weight of 311.9.

CLINICAL PHARMACOLOGY

Cyclobenzaprine HCl relieves skeletal muscle spasm of local origin without interfering with muscle

function. It is ineffective in muscle spasm due to central nervous system disease.

INDICATIONS AND USAGE

Cyclobenzaprine hydrochloride tablets,USP are indicated as an adjunct to rest and physical therapy for

relief of muscle spasm associated with acute, painful muscoskeletal conditions.

CONTRAINDICATIONS

Hypersensitivity to any component of this product. Concomitant use of monoamine oxidase (MAO)

inhibitors or within 14 days after their discontinuation.

WARNINGS

Serotonin Syndrome. The development of a potentially life-threatening serotonin syndrome has been

reported with Cyclobenzaprine hydrochloride when used in combination with other drugs, such as selective

serotonin reuptake inhibitors (SSRIs), serotonin norepinephrine reuptake inhibitors (SNRIs), tricyclic

antidepressants (TCAs), tramadol, bupropion, meperidine, verapimal,, or (MAO) inhibitors.

PRECAUTIONS

General. Because of its atropine - like action, cyclobenzaprine hydrochloride should be sued with caution

in patients with a history of urinary retention, angle-closure glaucoma, increased intraocular pressure and

in patients taking anticholinergic medication.

ADVERSE REACTIONS

Incidence of most common adverse reactions in the 2 double-blind, placebo controlled - 5 mg studies

(incidence of >3% on cyclobenzaprine hydrochloride 5 mg

DRUG ABUSE AND DEPENDENCE

Pharmacologic similarities among the tricyclic drugs require that certain withdrawal symptoms be

considered when cyclobenzaprine hydrochloride is administered, even though they have not been reported

to occur with this drug. Abrupt cessation of treatment after prolonged administration rarely may

produce nausea, headache and malaise. These are not indicative of addiction.

OVERDOSAGE

Although rare, deaths may occur from overdosage with cyclobenzaprine hydrochloride.

DOSAGE AND ADMINISTRATION

For most patients, the recommended dose of cyclobenzaprine hydrochloride tablets, USP is 5 mg three

times a day.

HOW SUPPLIED

Cyclobenzaprine hydrochloride tablets, USP 5 mg are supplied as butterscotch yellow-colored, capsule-

shaped, film-coated convex tablets, debossed with "AN40" on one side and plain on the other side.